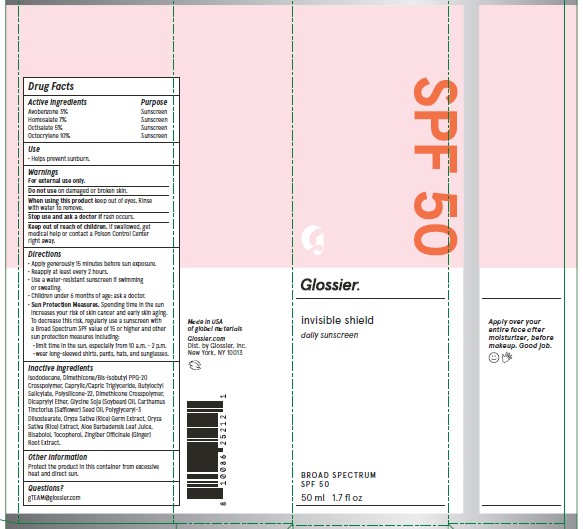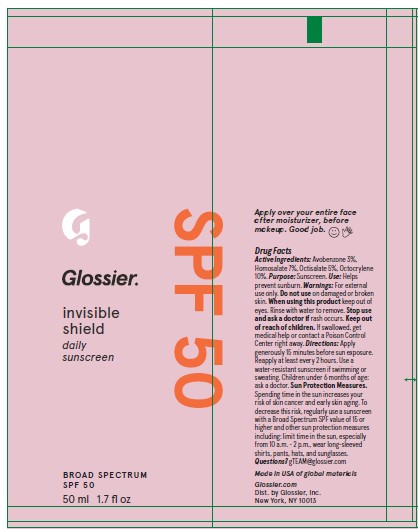 DRUG LABEL: Glossier Invisible Shield SPF 50
NDC: 51514-0368 | Form: GEL
Manufacturer: Autumn Harp
Category: otc | Type: HUMAN OTC DRUG LABEL
Date: 20240612

ACTIVE INGREDIENTS: AVOBENZONE 3 g/100 g; OCTISALATE 5 g/100 g; HOMOSALATE 7 g/100 g; OCTOCRYLENE 10 g/100 g
INACTIVE INGREDIENTS: ISODODECANE; .ALPHA.-TOCOPHEROL, DL-; POLYGLYCERYL-3 DIISOSTEARATE; MEDIUM-CHAIN TRIGLYCERIDES; DIMETHICONE/BIS-ISOBUTYL PPG-20 CROSSPOLYMER; ALOE VERA LEAF; DIMETHICONE/VINYL DIMETHICONE CROSSPOLYMER (SOFT PARTICLE); BUTYLOCTYL SALICYLATE; POLYMETHYLSILSESQUIOXANE (4.5 MICRONS); SAFFLOWER OIL; FARNESOL; SOYBEAN OIL; DICAPRYLYL ETHER; RICE GERM; .ALPHA.-BISABOLOL, (+/-)-; GINGER

Glossier Invisible Shield SPF 50

ACTIVE INGREDIENT

Avobenzone 3% - Sunscreen

Homosalate 7% - Sunscreen

Octisalae 5% - Sunscreen

Octocrylene 10% - Sunscreen

PURPOSE

Use: Helps prevent sunburn

WARNINGS

For external use only

Do not use on damaged or broken skin

When using this product keep out of eyes, Rinse with water to remove.

Stop use and ask a doctor if rash occurs.

Keep out of reach of children. If swallowed. get medical help or contact a Poison Control Center right away.

Keep out of reach of children. If swallowed, get medical help or contact a Poison Control Center right away.

INSTRUCTIONS FOR USE

Apply generously 15 minutes before sun exposure.

Reapply at least every 2 hours.

Use a water-resistant sunscreen if swimming or sweating.

Children under 6 months of age: ask a doctor.

Sun Protection Measures. Spending time in the sun increases your risk of skin cancer and early skin aging. To decrease this risk, regularly use a sunscreen with a Broad Spectrum SPF value of 15 or higher and other sun protection measures including:

- Limit time in the sun, especially from 10 a.m. - 2p.m.

- wear long-sleeved shirts, pants, hats, and sunglasses.

INACTIVE INGREDIENT

Inactive Ingredients: Isododecane, Dimethicone/Bis-Isobutyl PPG-20 Crosspolymer, Caprylic/Capric Triglyceride, Butyloctyl Salicylate, Polysilicone-22, Dimethicone Crosspolymer, Dicaprylyl Ether, Glycine Soja (Soybean) Oil, Carthamus Tinctorius (Safflower) Seed Oil, Polyglyceryl-3 Diisostearate, Oryza Sativa (Rice) Extract, Oryza Sativa (Rice) Germ Extract, Aloe Barbadensis Leaf Extract, Bisabolol, Tocopherol, Zingiber Officinale (Ginger) Root Extract.

OTHER SAFETY INFORMATION

Protect the product in this container from excessive heat and direct sun.

QUESTIONS

gTEAM@glossier.com

DOSAGE AND ADMINISTRATION

Apply generously 15 minutes before sun exposure. Reapply at least every 2 hours. Use a water resistant sunscreen if swimming or sweating. Children under 6 months of age: ask a doctor.

INDICATIONS AND USAGE

For external use only.

Do not use on damaged or broken skin.

When using this product keep out of eyes. Rinse with water to remove.

Stop use and ask a doctor if rash occurs.

Other information: Protect the product in this container from excessive heat and direct sun.